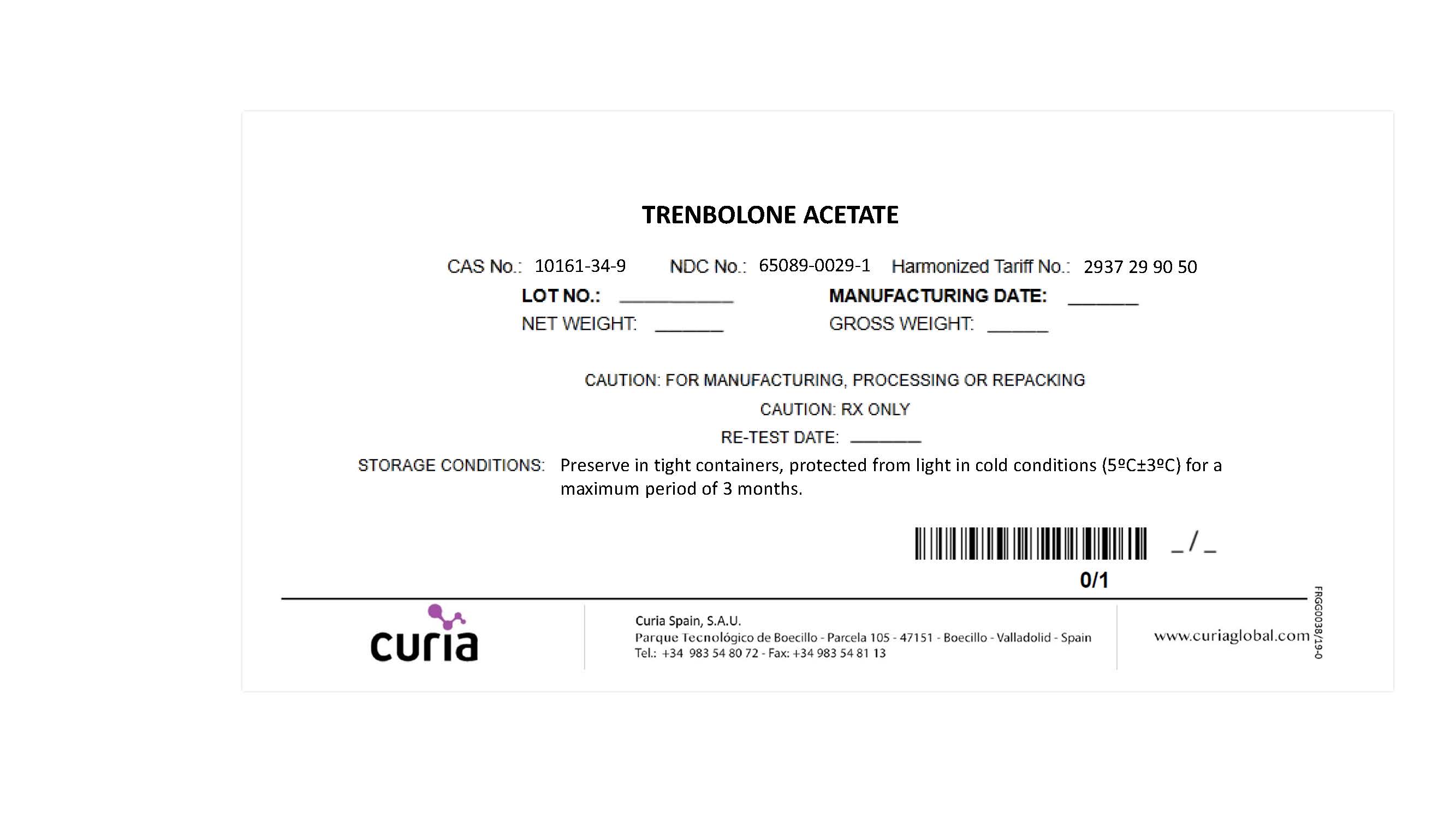 DRUG LABEL: Trenbolone acetate
NDC: 65089-0029 | Form: POWDER
Manufacturer: Curia Spain S.A.U.
Category: other | Type: BULK INGREDIENT
Date: 20211021
DEA Schedule: CIII

ACTIVE INGREDIENTS: TRENBOLONE ACETATE 1 kg/1 kg

Trenbolone acetate